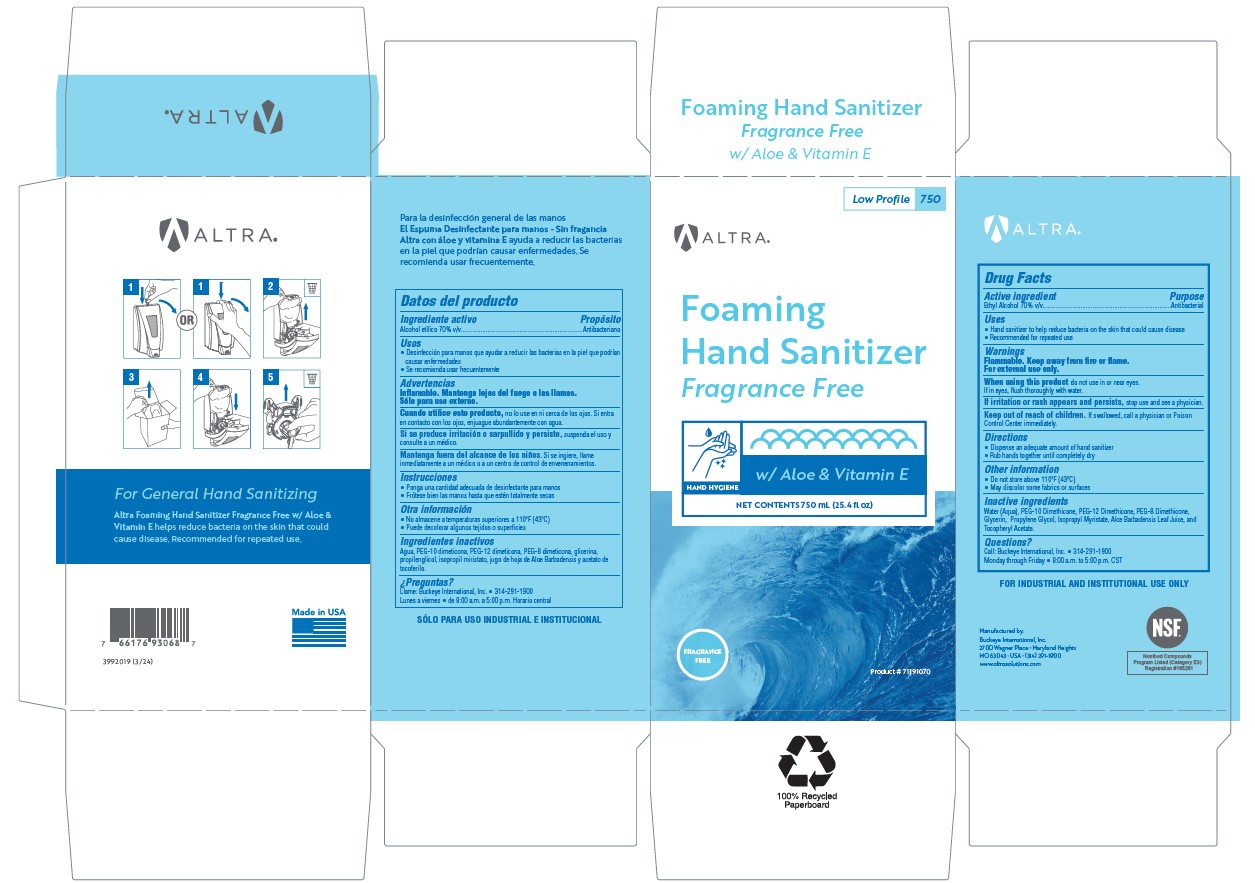 DRUG LABEL: Altra Foaming Hand Sanitizer Fragrance Free with Aloe and Vitamin E
NDC: 30805-023 | Form: LIQUID
Manufacturer: Buckeye International, Inc.
Category: otc | Type: HUMAN OTC DRUG LABEL
Date: 20250327

ACTIVE INGREDIENTS: ALCOHOL 70 mL/100 mL
INACTIVE INGREDIENTS: WATER; GLYCERIN; ALOE VERA LEAF; PROPYLENE GLYCOL; .ALPHA.-TOCOPHEROL ACETATE; ISOPROPYL MYRISTATE; PEG-12 DIMETHICONE (300 CST); PEG-8 DIMETHICONE; PEG-10 DIMETHICONE (600 CST)

Drug Facts 30805-023

Active ingredient

Ethyl Alcohol 70% v/v

Purpose

Antibacterial

Uses

- Hand sanitizer to help reduce bacterial on skin that could cause disease
- Recommended for repeated use

Warnings

Flammable. Keep away from fire or flame.

For external use only.

When using this product do not use in or near eyes.

If in eyes, flush thoroughly with water.

STOP USE

If irritation or rash appears and persists, stop use and see a physician

Keep out of reach of children. If swallowed, call a physician or Poison Control Center immediately.

Directions

- Dispense an adequate amount of hand sanitizer
- Rub Hands together until completely dry

Other information

- Do not store above 110°F (43°C)
- May discolor some fabrics or surfaces

Inactive ingredients

Water (Aqua), PEG-10 Dimethicone, PEG-12 Dimethicone, PEG-8 Dimethicone, Glycerine, Propylene Glycol, Isopropyl Myristate, Aloe Barbadensis Leaf Juice, and Tocopheryl Acetate.

Questions?

Call: Buckeye International, Inc. • 314-291-1900

Monday through Friday • 8:00 a.m. to 5:00 p.m. CST

PACKAGE LABEL

ALTRA

Foaming

Hand Sanitizer

Fragrance Free

HAND HYGIENE

w/ Aloe & Vitamin E

NET CONTENTS 750 mL (25.4 fl oz)

FRAGRANCE FREE